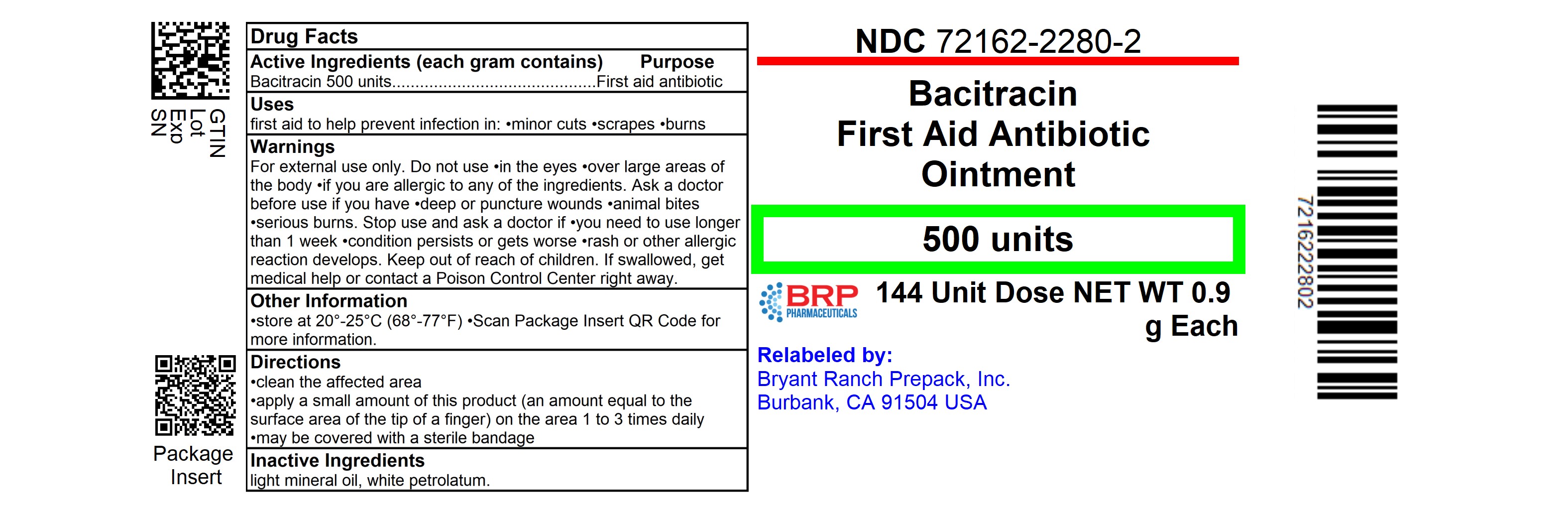 DRUG LABEL: Bacitracin
NDC: 72162-2280 | Form: OINTMENT
Manufacturer: Bryant Ranch Prepack
Category: otc | Type: HUMAN OTC DRUG LABEL
Date: 20251201

ACTIVE INGREDIENTS: BACITRACIN 500 [USP'U]/1 g
INACTIVE INGREDIENTS: LIGHT MINERAL OIL; PETROLATUM

Bacitracin Drug Facts

Active ingredient (each gram contains)

Bacitracin 500 units

Purpose

First aid antibiotic

Uses

first aid to help prevent infection in:

- minor cuts
- scrapes
- burns

Warnings

For external use only

Do not use

- in the eyes
- over large areas of the body
- if you are allergic to any of the ingredients

Ask a doctor before use if you have

- deep or puncture wounds
- animal bites
- serious burns

Stop use and ask a doctor if

- you need to use longer than 1 week
- condition persists or gets worse
- rash or other allergic reaction develops

Keep out of reach of children.

If swallowed, get medical help or contact a Poison Control Center right away. (1-800-222-1222)

Directions

- clean the affected area
- apply a small amount of this product (an amount equal to the surface area of the tip of a finger) on the area 1 to 3 times daily
- may be covered with a sterile bandage

Other information

- store at 20°-25°C (68°-77°F)

Inactive ingredients

light mineral oil, white petrolatum

Questions or comments?

1-800-719-9260

HOW SUPPLIED

Bacitracin First Aid Antibiotic Ointment

- NDC 72162-2280-2: 144 Unit dose

Repackaged/Relabeled by:
Bryant Ranch Prepack, Inc.
Burbank, CA 91504

PACKAGE LABEL

Bacitracin First Aid Antibiotic Ointment

144 Unit Dose

NET WT 0.9 g Each